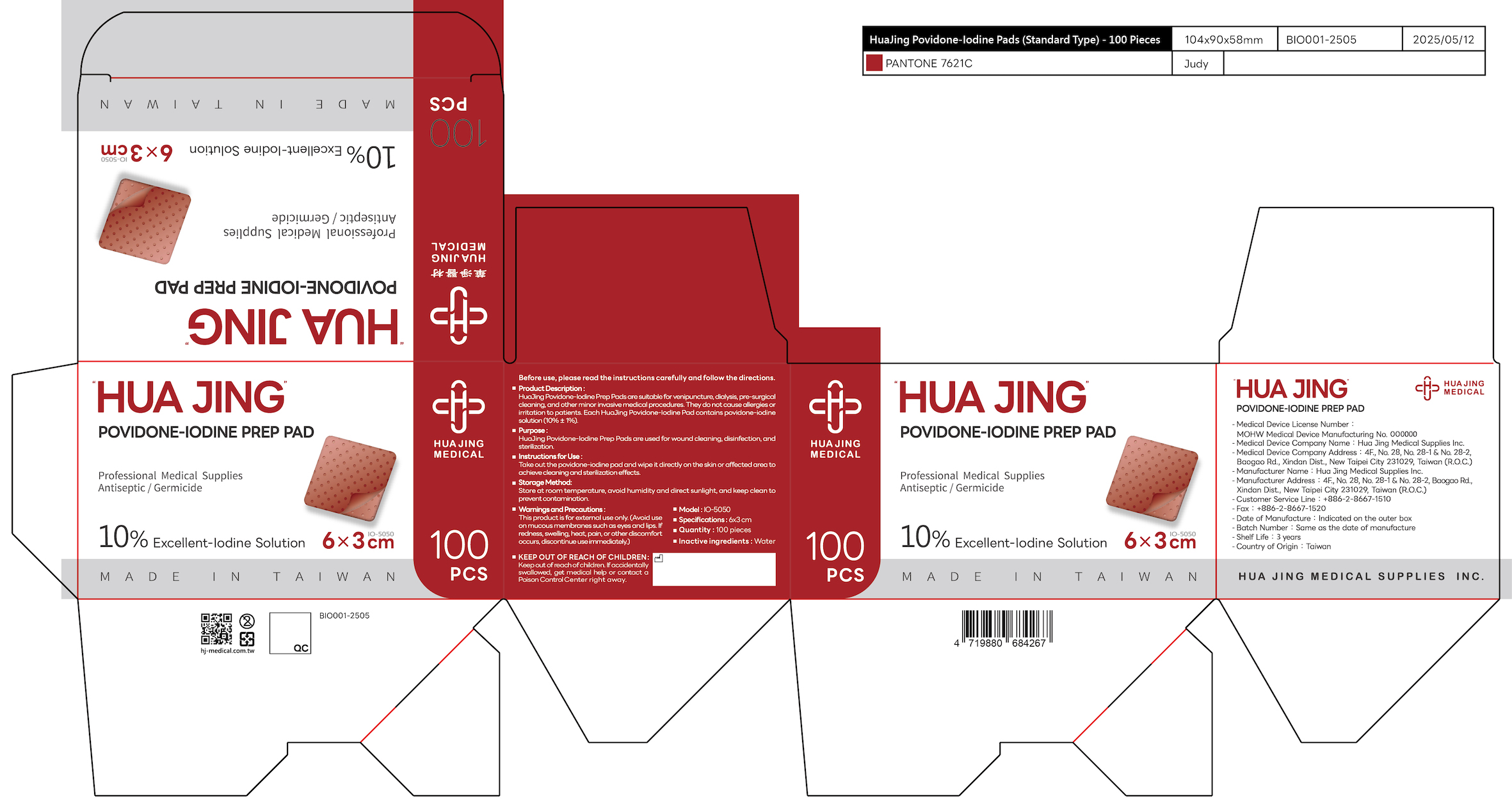 DRUG LABEL: Povidone Iodine Prep Pad
NDC: 83170-003 | Form: CLOTH
Manufacturer: Hua Jing Medical Supplies INC.
Category: otc | Type: HUMAN OTC DRUG LABEL
Date: 20260210

ACTIVE INGREDIENTS: POVIDONE-IODINE 10 mg/100 mg
INACTIVE INGREDIENTS: WATER

83170-003-02, Hua Jing Povidone-Iodine Prep Pad

Povidone Iodine Prep Pad, Package NDC: 83170-003-01

Active Ingredient(s): 10% Povidone-iodine Solution

Purpose

HuaJing Povidone-Iodine Prep Pads are suitable for venipuncture, dialysis, pre-surgical cleaning, and other minor invasive medical procedures. They do not cause allergies or irritation to patients. Each HuaJing Povidone-Iodine Pad contains povidone-iodine solution (10%±1%).

Use

Instructions for Use:

Take out the povidone-iodine pad and wipe directly on the skin, hands, or instruments to achieve cleaning and sterilization effects.

Warnings

Warnings and Precautions:

This product is for external use only. (Avoid use on mucous membranes such as eyes and lips. If redness, swelling, heat, pain, or other discomfort occurs, discontinue use immediately.)

Keep out of reach of children. If accidentally swallowed, get medical help or contact a Poison Control Center right away.

Inactive ingredients

Inactive ingredients: Water

Product Description

HuaJing Povidone-Iodine Prep Pads are suitable for venipuncture, dialysis, pre-surgical cleaning, and other minor invasive medical procedures. They do not cause allergies or irritation to patients. Each HuaJing Povidone-Iodine Pad contains povidone-iodine solution (10%±1%).

Model: IO-5050

Specifications: 6x3 cm

Quantity: 100 pieces

Hua Jing Povidone-Iodine Prep Pad, Package NDC: 83170-003-01